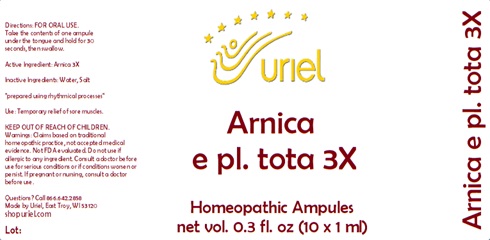 DRUG LABEL: Arnica e pl. tota 3
NDC: 48951-1126 | Form: LIQUID
Manufacturer: Uriel Pharmacy Inc.
Category: homeopathic | Type: HUMAN OTC DRUG LABEL
Date: 20240401

ACTIVE INGREDIENTS: ARNICA MONTANA 3 [hp_X]/1 mL
INACTIVE INGREDIENTS: WATER; SODIUM CHLORIDE

Arnica e pl. tota 3

INDICATIONS AND USAGE

Directions: FOR ORAL USE.

DOSAGE AND ADMINISTRATION

Take the contents of one ampule under the tongue and hold for 30 seconds, then swallow.

Active Ingredient: Arnica 3X

Inactive Ingredients: Water, Salt

PURPOSE

Use: Temporary relief of sore muscles.

KEEP OUT OF REACH OF CHILDREN.

WARNINGS

Warnings: Claims based on traditional homeopathic practice, not accepted medical evidence. Not FDA evaluated. Do not use if allergic to any ingredient. Consult a doctor before use for serious conditions or if conditions worsen or persist. If pregnant or nursing, consult a doctor before use.

Questions? Call 866.642.2858
Uriel, East Troy, WI 53120
shopuriel.com Lot: